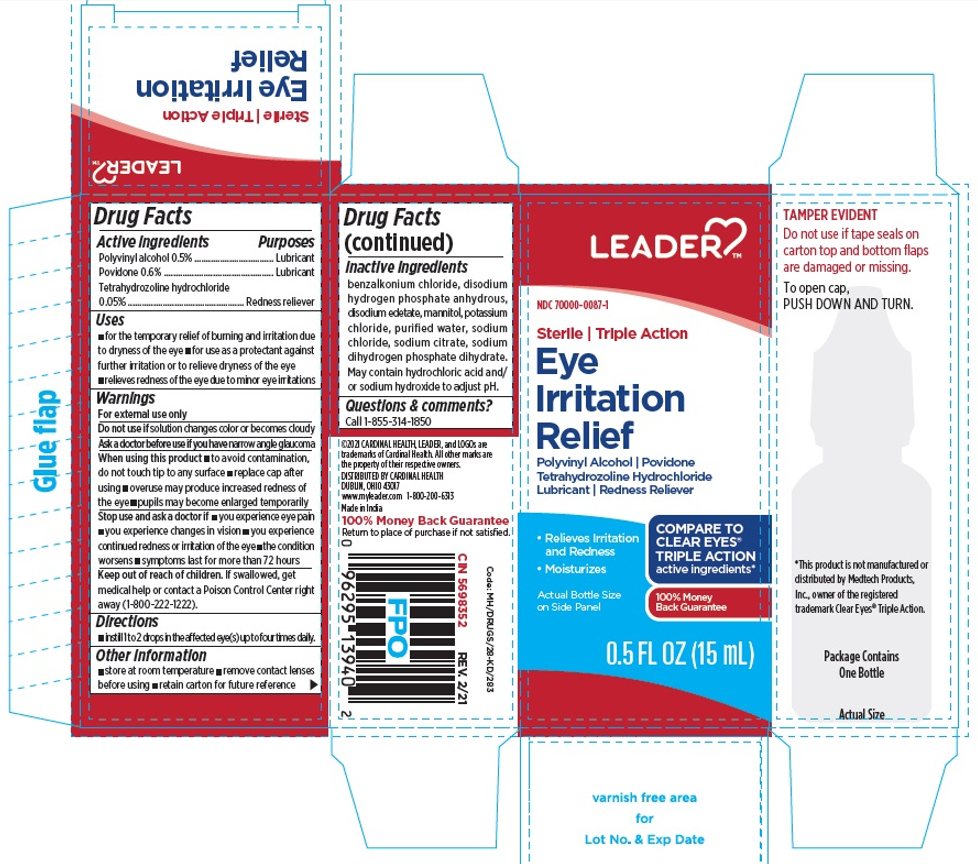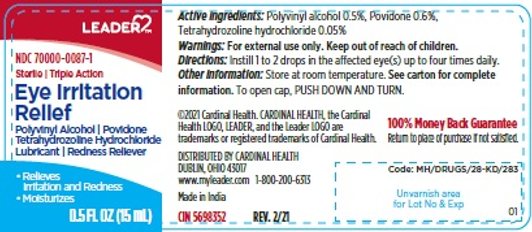 DRUG LABEL: Eyes Irritation Relief
NDC: 70000-0087 | Form: LIQUID
Manufacturer: CARDINAL HEALTH 110, LLC. DBA LEADER
Category: otc | Type: HUMAN OTC DRUG LABEL
Date: 20250912

ACTIVE INGREDIENTS: POLYVINYL ALCOHOL, UNSPECIFIED 5 mg/1 mL; POVIDONE, UNSPECIFIED 6 mg/1 mL; TETRAHYDROZOLINE HYDROCHLORIDE 0.5 mg/1 mL
INACTIVE INGREDIENTS: BENZALKONIUM CHLORIDE; SODIUM PHOSPHATE, DIBASIC, ANHYDROUS; EDETATE DISODIUM; MANNITOL; POTASSIUM CHLORIDE; WATER; SODIUM HYDROXIDE; SODIUM CITRATE, UNSPECIFIED FORM; SODIUM PHOSPHATE, MONOBASIC, DIHYDRATE

Sterile Eyes Irritation Relief Triple Action

Drug Facts

Active ingredients

Polyvinyl alcohol 0.5%

Active ingredients

Povidone 0.6%

Purpose

Lubricant

Active ingredient

Tetrahydrozoline hydrochloride 0.05%

Purpose

Redness reliever

Uses

- for the temporary relief of burning & irritation due to dryness of the eye
- for use as a protectant against further irritation or to relieve dryness of the eye
- relieves redness of the eye due to minor eye irritations

Warnings

For external use only

Do not use if

solution changes color or becomes cloudy.

Ask a doctor before use if you have

narrow angle glaucoma.

When using this product

- to avoid contamination, do not touch tip to any surface
- replace cap after using
- overuse may produce increased redness of the eye
- pupils may become enlarged temporarily

Stop use & ask a doctor if

- you experience eye pain
- you experience changes in vision
- you experience continued redness or irritation of the eye
- the condition worsens
- symptoms last for more than 72 hours

Keep out of reach of children.

If swallowed, get medical help or contact a Poison Control Center(1-800-222-1222) right away.

Directions

Instill 1 to 2 drops in the affected eye(s) up to four times daily.

Other information

- store at room temperature
- remove contact lenses before using

Inactive ingredients

Benzalkonium Chloride, Disodium Hydrogen Phosphate Anhydrous, Disodium Edetate, Mannitol , Potassium Chloride, Purified Water, Sodium dihydrogen Phosphate Dihydrate, Sodium Chloride, Sodium Citrate , May Contain Hydrochloric Acid and/or Sodium Hydroxide to Adjust PH.

.

TAMPER EVIDENT

Do not use if tape seals on carton top and bottom flaps are damaged or missing

To open cap, PUSH DOWN AND TURN.

*This product is not manufactured or distributed by Medtech Products, Inc., owner of the registered trademark Clear Eyes® Triple Action.

DISTRIBUTED BY CARDINAL HEALTH

DUBLIN, OHIO 43017

www.myleader.com 1-800-200-6313

Made in India

100% Money Back Guarantee

Return to place of purchase if not satisfied.

Code: MH/DRUGS/28-KD/283

CIN 5698352 | REV. 2/21

Principal Display Panel

LEADER™

NDC 70000-0087-1

Sterile / Triple Action

Eye Irritation

Relief

Polyvinyl Alcohol / Povidone

Tetrahydrozoline Hydrochloride

Lubricant / Redness Reliever

- Relieves Irritation and Redness
- Moisturizes

0.5 FL OZ (15 mL)

Principal Display Panel

LEADER™

NDC 70000-0087-1

Sterile / Triple Action

Eye

Irritation

Relief

Polyvinyl Alcohol / Povidone

Tetrahydrozoline Hydrochloride

Lubricant / Redness Reliever

- Relieves Irritation and Redness
- Moisturizes

Actual Bottle Size on Side Panel

COMPARE TO CLEAR EYES® TRIPLE ACTION active ingredients*

100% Money Back Guarantee

0.5 FL OZ (15 mL)